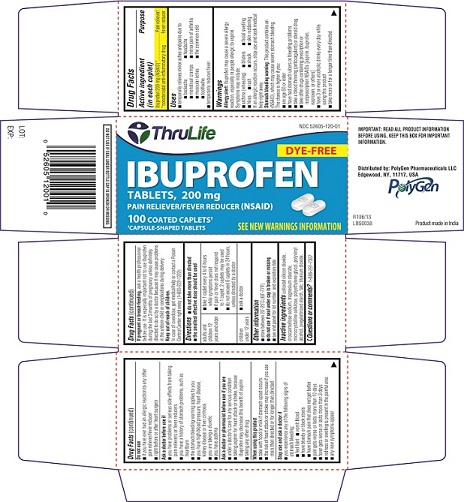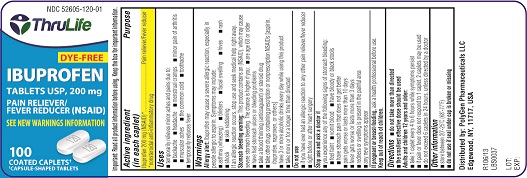 DRUG LABEL: Ibuprofen
NDC: 52605-120 | Form: TABLET
Manufacturer: Polygen Pharmaceuticals LLC
Category: otc | Type: Human OTC Drug Label
Date: 20130701

ACTIVE INGREDIENTS: IBUPROFEN 200 mg/1 1
INACTIVE INGREDIENTS: CELLULOSE, MICROCRYSTALLINE; CROSCARMELLOSE SODIUM; TALC; MAGNESIUM STEARATE; STARCH, CORN; COLLOIDAL SILICON DIOXIDE; POLYETHYLENE GLYCOLS; POLYVINYL ALCOHOL; TITANIUM DIOXIDE

ACTIVE INGREDIENT(S)

(each Caplet contains)

Ibuprofen 200 mg (NSAID)*

· Non-steroidal anti-inflammatory drug

PURPOSE

Pain reliever / fever reducer

USE(S)

- temporarily relieves minor aches and pain due to :
- backache
- headache
- menstrual cramps
- minor pain of arthritis
- muscular aches
- the common cold
- toothache
- temporarily reduces fever

WARNINGS

Allergy alerts: Ibuprofen may cause a severe allergy reaction, especially in people allergic to aspirin.

Symptoms may include:

- asthma (wheezing)
- blisters
- facial swelling
- hives
- rash
- shock
- skin reddening

If an allergic reaction occurs, stop use and seek medical help right away.

Stomach bleeding warning: This product contains a nonsteroidal anti-inflammatory drug (NSAID), which may cause stomach bleeding. The chance is higher if you:

- are age 60 or older
- have bad stomach ulcers or bleeding problems
- take a blood thinning (anticoagulant) or steroid drug
- take other drug containing prescription NSAID (aspirin, ibuprofen, naproxen, or others)
- have 3 or more alcoholic drinks every day while using this product
- the more or for a longer time than directed

DO NOT USE

- if you have ever had an allergic reaction to any other pain reliever/fever reducer
- right before or after heart surgery

ASK A DOCTOR BEFORE USE IF

You have

- problems or serious side effects from taking pain relievers or fever reducers
- stomach problems that last or come back, such as heartburn, upset stomach, or stomach pain
- ulcers
- bleeding problems
- high blood pressure
- heart or kidney disease
- taken a diuretics
- reached age 60 or older

ASK A DOCTOR OR PHARMACIST BEFORE USE IF

You are

- taking any other drugs containing an NSAID (prescription or nonprescription)
- taking a blood thinning (anticoagulant) or steroid drug
- under a doctor’s care for any serious condition
- taking aspirin for heart attacks or stroke, because ibuprofen may decrease this benefit of aspirin
- taking any other drug

WHEN USING THIS PRODUCT

- take with food or milk if stomach upset occurs
- long term continuous use may increase the risk of heart attack or stroke

STOP USE AND ASK DOCTOR IF

- You feel faint, vomit blood, or have bloody or black stools.

These are signs of stomach bleeding.

- pain gets worse or lasts more than 10 days
- fever gets worse or lasts more than 3 days
- stomach pain or upset gets worse or lasts
- redness or swelling is present in painful area
- any new symptoms appear

PREGNANCY/BREASTFEEDING

Ask a health professional before use. It is especially important not to use ibuprofen during the last 3 months of pregnancy unless definitely directed to do so by a doctor because it may cause a problems in the unborn child or complications during delivery.

KEEP OUT OF REACH OF CHILDREN

In case of overdose, get medical help or contact a PoisonControlCenter right away.

DIRECTIONS

- do not take more than directed
- the smallest effective dose should be used
- do not take longer than 10 days, unless directed by a doctor
  (see Warnings)

adults and children 12 years and older | - take 1 caplet every 4 to 6 hours while symptoms persist - if pain or fever does not respond to 1 caplet, 2 caplets may be used - do not exceed 6 caplets in 24 hours, unless directed by a doctor.
Children under 12 years | - ask a doctor

STORAGE

- Store between 20-25^0C (68-77^0F).
- do not use if seal under bottle cap is broken or missing.

INACTIVE INGREDIENTS

Microcrystalline Cellulose, Croscarmellose Sodium, Pregelatinized starch, talc, Colloidal silicon dioxide, Magnesium stearate,polyvinyl Alcohol, Polyethylene glycol,Titanium dioxide.

PRINCIPAL DISPLAY PANEL

Carton Label
Thrulife
NDC : 52605-120-01
IBUPROFEN TABLETS, 200 mg
PAIN RELIEVER/ FEVER REDUCER (NSAID)
100 COATED CAPLETS
CAPSULE SHAPED TABLETS
Bottle label PDP
Thrulife
NDC:52605-120-01
IBUPROFEN TABLETS USP, 200 mg
PAIN RELIEVER/ FEVER REDUCER (NSAID)
100 COATED CAPLETS
CAPSULE SHAPED TABLETS